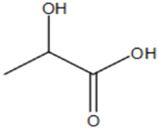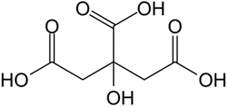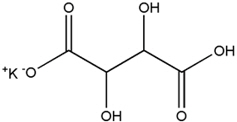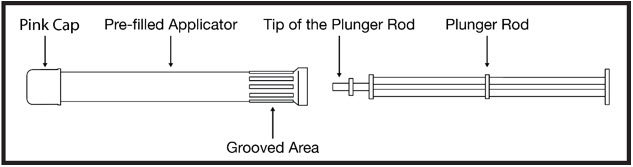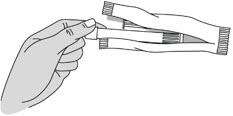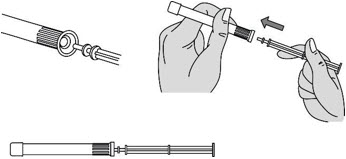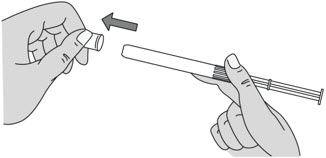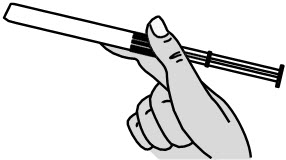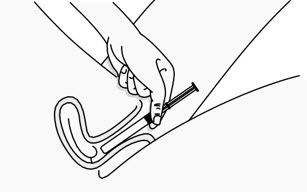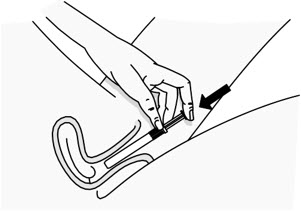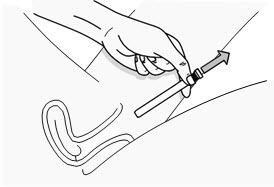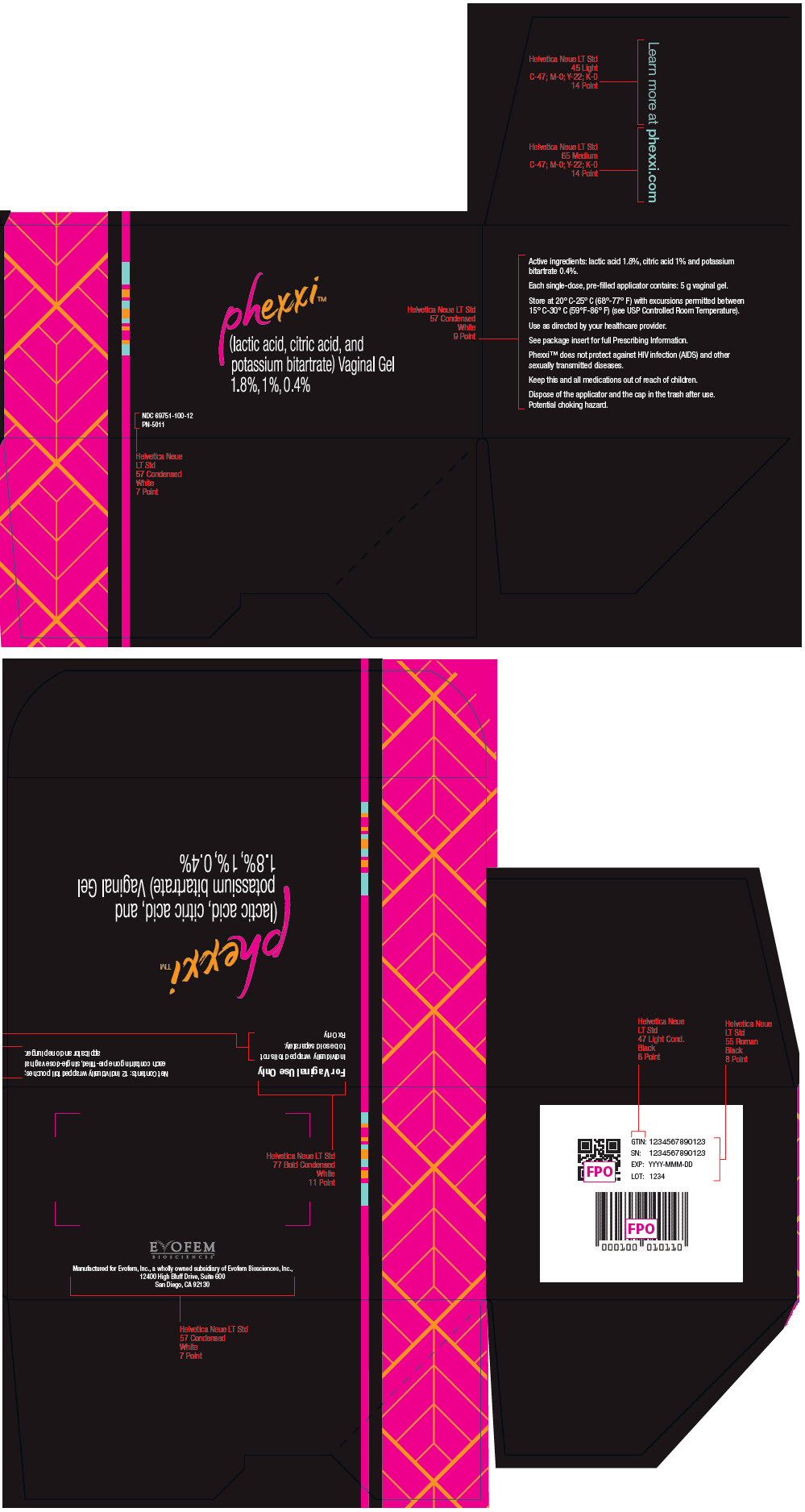 DRUG LABEL: Phexxi
NDC: 69751-100 | Form: GEL
Manufacturer: Evofem, Inc.
Category: prescription | Type: HUMAN PRESCRIPTION DRUG LABEL
Date: 20231121

ACTIVE INGREDIENTS: LACTIC ACID, L- 90 mg/5 g; CITRIC ACID MONOHYDRATE 50 mg/5 g; POTASSIUM BITARTRATE 20 mg/5 g

HIGHLIGHTS OF PRESCRIBING INFORMATION

These highlights do not include all the information needed to use PHEXXI ® safely and effectively. See full prescribing information for PHEXXI.
PHEXXI (lactic acid, citric acid, and potassium bitartrate) vaginal gel
Initial U.S. Approval: 2020

1 INDICATIONS AND USAGE

PHEXXI is a combination of lactic acid, citric acid, and potassium bitartrate indicated for the prevention of pregnancy in females of reproductive potential for use as an on-demand method of contraception. (1)

Limitations of Use: PHEXXI is not effective for the prevention of pregnancy when administered after intercourse.

2 DOSAGE AND ADMINISTRATION

- Administer one (1) pre-filled single-dose applicator of PHEXXI (5 grams) vaginally immediately before (or up to one hour before) each episode of vaginal intercourse (2.1)
- May use during any part of the menstrual cycle (2.2)

3 DOSAGE FORMS AND STRENGTHS

Each pre-filled single-dose vaginal applicator delivers 5 grams of gel containing lactic acid (1.8%), citric acid (1%), and potassium bitartrate (0.4%). (3)

5 WARNINGS AND PRECAUTIONS

- Cystitis and Pyelonephritis: Avoid use in women with a history of recurrent UTI or urinary tract abnormalities (5.1)

6 ADVERSE REACTIONS

Most common adverse reactions (≥2%) were vulvovaginal burning sensation, vulvovaginal pruritus, vulvovaginal mycotic infection, urinary tract infection, vulvovaginal discomfort, bacterial vaginosis, vaginal discharge, genital discomfort, dysuria, and vulvovaginal pain. (6.1)

To report SUSPECTED ADVERSE REACTIONS, contact Evofem at toll-free phone 1-833-EVFMBIO or FDA at 1-800-FDA-1088 or www.fda.gov/medwatch.

FULL PRESCRIBING INFORMATION

1 INDICATIONS AND USAGE

PHEXXI is indicated for the prevention of pregnancy in females of reproductive potential for use as an on-demand method of contraception.

Limitations of Use

PHEXXI is not effective for the prevention of pregnancy when administered after intercourse [see Dosage and Administration (2.1)].

2 DOSAGE AND ADMINISTRATION

2.1 Recommended Dosage

Administer one pre-filled applicator of PHEXXI (5 grams) vaginally immediately before or up to one hour before each act of vaginal intercourse. If more than one act of vaginal intercourse occurs within one hour, an additional dose must be applied. Five grams of PHEXXI contains 90 mg of lactic acid, 50 mg of citric acid, and 20 mg of potassium bitartrate.

2.2 Timing of PHEXXI Use

May use PHEXXI during any part of the menstrual cycle. May use PHEXXI as soon as it is safe to resume vaginal intercourse after childbirth, abortion, or miscarriage.

2.3 Use of PHEXXI with Other Contraceptive Methods

PHEXXI may be used concomitantly with hormonal contraceptives; latex, polyurethane, and polyisoprene condoms; and vaginal diaphragms. Avoid PHEXXI use with vaginal rings.

2.4 Use of PHEXXI with Other Vaginal Products

PHEXXI may be used concomitantly with other products for vaginal infections including miconazole, metronidazole, and tioconazole.

3 DOSAGE FORMS AND STRENGTHS

Vaginal gel: 18 mg of lactic acid, 10 mg of citric acid, and 4 mg of potassium bitartrate in each gram (1.8%, 1%, and 0.4%, respectively) of off-white to tan color gel supplied in a pre-filled single-dose (5 grams) vaginal applicator

5 WARNINGS AND PRECAUTIONS

5.1 Cystitis and Pyelonephritis

Among 2804 subjects who received PHEXXI in Studies 1 and 2, 0.36% (n=10) reported adverse reactions of cystitis, pyelonephritis, or other upper urinary tract infection (UTI). Of these, one case of pyelonephritis was considered serious and required hospitalization. Avoid use of PHEXXI in females of reproductive potential with a history of recurrent urinary tract infection or urinary tract abnormalities.

6 ADVERSE REACTIONS

The following clinically significant adverse reactions are described elsewhere in the labeling:

- Cystitis and Pyelonephritis [see Warnings and Precautions (5.1)]

6.1 Clinical Trials Experience

Because clinical trials are conducted under widely varying conditions, adverse reaction rates observed in the clinical trials of a drug cannot be directly compared to rates in the clinical trials of another drug and may not reflect the rates observed in practice.

The safety of PHEXXI (pre-filled applicator with 5-gram dose) has been evaluated in two clinical trials (Study 1 and Study 2) in 2804 subjects (over 19,000 cycles of exposure). The racial/ethnic distribution was 66% White, 27% Black or African American, 2% Asian, 1% American Indian or Alaska Native, 0.3% Native Hawaiian or Pacific Islander, and 5% other; 32% of the study population was Hispanic. Study 1 included a one-year extension phase where 342 U.S. subjects were exposed to PHEXXI for 13 cycles.

Hypersensitivity Reaction

Of the 2804 PHEXXI-treated subjects in Studies 1 and 2, one subject reported a suspected drug hypersensitivity. Avoid PHEXXI use in females of reproductive potential with suspected hypersensitivity to the ingredients in PHEXXI.

The most common adverse reactions (≥10%) in the U.S. population in Studies 1 and 2 (n = 2480) were: vulvovaginal burning sensation (18.0%) and vulvovaginal pruritus (14.5%). The majority of these adverse reactions were mild and few led to discontinuation. Table 1 summarizes the most common adverse reactions (≥2%) reported by subjects using PHEXXI in the U.S.

Table 1. Adverse Reactions that Occurred in ≥ 2% of Subjects Who Used PHEXXI to Prevent Pregnancy (Studies 1 and 2 – U.S. population only)
Adverse Reaction | PHEXXI (N=2480) (%)
Vulvovaginal Burning Sensation | 18.0
Vulvovaginal Pruritus | 14.5
Vulvovaginal Mycotic Infection [Includes preferred terms (PT) vulvovaginal mycotic infection and vulvovaginal candidiasis.] | 9.1
Urinary Tract Infection [Includes PTs urinary tract infection, streptococcal urinary tract infection, Escherichia urinary tract infection, and urinary tract infection bacterial.] [Does not include PTs cystitis, kidney infection, and pyelonephritis [see Warnings and Precautions (5.1)].] | 9.0
Vulvovaginal Discomfort | 9.0
Bacterial Vaginosis | 8.4
Vaginal Discharge | 5.5
Genital Discomfort | 4.1
Dysuria | 3.1
Vulvovaginal pain | 2.1

Among subjects who used PHEXXI in Studies 1 and 2, 1.6% discontinued from the clinical trials due to an adverse reaction. The most common adverse reactions leading to study discontinuation were vulvovaginal burning sensation (0.7%); and vulvovaginal pruritus and vulvovaginal discomfort (0.1% each).

Adverse Reactions in Male Partners

Among male partners of subjects who used PHEXXI for contraception in Study 2, 9.8% (131 of 1330) reported symptoms of local discomfort (burning, itching, pain, and "other"). Of these local discomfort symptoms, 74.7% were mild, 21.4% were moderate, and 3.9% were severe. Two subjects discontinued participation in the study due to male partner symptoms.

8 USE IN SPECIFIC POPULATIONS

8.1 Pregnancy

Risk Summary

There is no use for PHEXXI in pregnancy; therefore, discontinue PHEXXI during pregnancy. There are no data with the use of PHEXXI in pregnant women or animals. In the U.S. general population, the estimated background risk of major birth defects and miscarriage in clinically recognized pregnancies is 2 to 4 percent and 15 to 20 percent, respectively.

8.2 Lactation

Risk Summary

There are no data on the presence of lactic acid, citric acid, and potassium bitartrate or their metabolites in human milk, the effects on the breastfed infant, or the effects on milk production.

8.4 Pediatric Use

The safety and effectiveness of PHEXXI have been established in females of reproductive potential. Efficacy is expected to be the same for post-menarchal females under the age of 17 as for users 17 years and older. The use of PHEXXI before menarche is not indicated.

11 DESCRIPTION

PHEXXI (lactic acid, citric acid, and potassium bitartrate) is a vaginal gel.

PHEXXI is an off-white to tan in color gel of uniform consistency, containing three active ingredients: lactic acid, citric acid, and potassium bitartrate.

The structural formula for lactic acid is:

Lactic acid is designated chemically as 2-hydroxypropanoic acid with an empirical formula of C3H6O3 and a molecular weight of 90.08 g/mol.

The structural formula for citric acid is:

Citric acid is designated chemically as 2-hydroxypropane-1,2,3-tricarboxylic acid with an empirical formula of C6H8O7 and a molecular weight of 192.124 g/mol.

The structural formula for potassium bitartrate is:

Potassium bitartrate is designated chemically as potassium; (2R, 3R)-2,3,4-trihydroxy-4-oxobutanoate with an empirical formula of KC4H5O6 and a molecular weight of 188.177 g/mol.

Each 5 gram dose is provided in a pre-filled single-dose applicator containing lactic acid USP (1.8% w/w), citric acid USP (1% w/w), and potassium bitartrate USP (0.4% w/w). Inactive ingredients present in the gel are: glycerin, alginic acid, xanthan gum, sodium hydroxide, benzoic acid, and purified water.

12 CLINICAL PHARMACOLOGY

12.1 Mechanism of Action

In in vitro studies, Phexxi produced a normal vaginal pH range (pH 3.5 – 4.5) in the presence of semen. In clinical studies, post-coital testing demonstrated pH < 5 in the majority of subjects, and sperm motility reduction.

12.2 Pharmacodynamics

Pharmacodynamic studies in humans have not been performed.

12.3 Pharmacokinetics

Pharmacokinetic studies in humans have not been performed. Systemic exposures of lactic acid, citric acid, and potassium bitartrate following vaginal administration of PHEXXI are not expected to lead to safety concerns.

In vitro studies with commonly used vaginal preparations (miconazole, metronidazole, tioconazole, and a product for maintaining normal vaginal pH) showed no significant effect on the pH or buffering capacity of PHEXXI.

13 NONCLINICAL TOXICOLOGY

13.1 Carcinogenesis, Mutagenesis, Impairment of Fertility

Carcinogenesis

Long-term carcinogenicity studies have not been performed with PHEXXI.

Mutagenesis

Mutagenic studies have not been performed with PHEXXI.

Impairment of Fertility

Reproductive studies have not been performed with PHEXXI. Upon discontinuation of PHEXXI, pregnancy may occur.

14 CLINICAL STUDIES

The efficacy of PHEXXI for the prevention of pregnancy was evaluated in a multi-center, open-label, single-arm clinical trial in the United States (AMP002; NCT03243305). The study enrolled females of reproductive potential 18 to 35 years of age with regular menstrual cycles (21 to 35 days). The median age was 27.8 years. The racial distribution was 70.6% White, 23.7% Black or African American, 2.5% Asian, 0.4% American Indian or Alaska Native, 0.2% Native Hawaiian or Pacific Islander, and 2.7% other. Subjects agreed to engage in at least 3 acts of heterosexual, vaginal intercourse per cycle. Subjects self-administered a 5 gram dose of PHEXXI intravaginally up to one hour before each episode of intercourse for up to 7 cycles.

The primary efficacy endpoint was the 7-cycle typical use cumulative pregnancy rate as derived by Kaplan-Meier life-table analysis. A total of 101 on-treatment pregnancies occurred in 1183 subjects contributing 4769 evaluable natural cycles. The 7-cycle cumulative pregnancy rate was 13.7% (95% CI: 10.0%, 17.5%), excluding cycles with back-up contraception, cycles <21 days or >35 days in length and cycles in which no intercourse was reported. The estimated Pearl Index, calculated based on data from the 7-cycle study, was 27.5 (95% CI: 22.4%, 33.5%).

16 HOW SUPPLIED/STORAGE AND HANDLING

PHEXXI (lactic acid, citric acid, and potassium bitartrate) vaginal gel is an off-white to tan color gel of uniform consistency containing lactic acid (1.8%), citric acid (1%), and potassium bitartrate (0.4%), supplied as individually wrapped 5 gram pre-filled single-dose vaginal applicators in sealed foil pouches along with a plunger, and are available as follows:

- NDC 69751-100-12 | Box of 12 units
- NDC 69751-100-03 | Sample box of 3 units

STORAGE AND HANDLING

Store in the original foil pack at room temperature 20°C to 25°C (68°F to 77°F); excursion permitted between 15°C to 30°C (59°F to 86°F) [see USP Controlled Room Temperature].

17 PATIENT COUNSELING INFORMATION

Advise the patient to read the Patient Information and FDA-approved patient labeling (Instructions for Use). Advise the patient:

- To intravaginally administer the contents of one pre-filled single-dose applicator of PHEXXI before each episode of vaginal intercourse and to administer an additional dose if intercourse does not occur within one hour of administration [see Dosage and Administration (2.1)].
- To consult their healthcare provider for severe or prolonged genital irritation [see Adverse Reactions (6.1)].
- To discontinue PHEXXI if they develop a local hypersensitivity reaction [see Adverse Reactions (6.1)].
- To contact their healthcare provider if experiencing urinary tract symptoms [see Warnings and Precautions (5.1)].
- That PHEXXI does not protect against HIV infection and other sexually transmitted infections.

Manufactured for Evofem, Inc., a wholly owned subsidiary of Evofem Biosciences, Inc., 12636 High Bluff Drive, Suite 400, San Diego, CA 92130
©2023 Evofem, Inc. All rights reserved.
U.S. Patents 6,706,276 and 10,568,855

PATIENT INFORMATION PHEXXI® (FEX ee)
(lactic acid, citric acid, and potassium bitartrate) vaginal gel
For Vaginal Use Only

What is PHEXXI?

- PHEXXI is a prescription medicine used to prevent pregnancy in females who can become pregnant and choose to use an on-demand method of birth control.
- PHEXXI is not effective at preventing pregnancy when used after vaginal sex.

How well does PHEXXI work?

Your chance of getting pregnant depends on how well you follow the directions for using PHEXXI. The better you follow the directions, the less chance you have of getting pregnant. It is very important that you follow the directions carefully each time you have vaginal sex.

PHEXXI does not protect against HIV infection or other sexually transmitted infections (STIs).

Before using PHEXXI, tell your healthcare provider about all of your medical conditions, including if you:

- are pregnant or think you are pregnant. PHEXXI is not for use in pregnant women.
- are breastfeeding or plan to breastfeed. It is not known if PHEXXI passes into your breast milk.

Tell your healthcare provider about all the medicines you take, including prescription and over-the-counter medicines, vitamins, and herbal supplements.

Know the medicines you take. Keep a list of them to show your healthcare provider and pharmacist when you get a new medicine.

How should I use PHEXXI?

- See the Instructions for Use that come with PHEXXI for detailed instructions on the right way to use PHEXXI.
- Use PHEXXI exactly as your healthcare provider tells you to use it.
- PHEXXI must be used before vaginal sex.
- PHEXXI comes as a pre-filled single-dose vaginal applicator.
- Insert 1 PHEXXI pre-filled applicator into your vagina and use PHEXXI within 1 hour before each time you have vaginal sex. If you do not have vaginal sex within 1 hour of using PHEXXI, you must insert a new PHEXXI pre-filled applicator.
- If you have vaginal sex more than 1 time within 1 hour, you must use a new PHEXXI pre-filled applicator.
- PHEXXI may be used at any time during the menstrual cycle.
- PHEXXI may be used as soon as your healthcare provider tells you it is safe for you to have vaginal sex after childbirth, abortion, or miscarriage.
- PHEXXI may be used with hormonal contraceptives; and latex, polyurethane and polyisoprene condoms. PHEXXI may be used with a vaginal diaphragm. Avoid using PHEXXI with contraceptive vaginal rings.
- PHEXXI may be used with other medicines used in the vagina to treat infections including miconazole, metronidazole and tioconazole.

What are the possible side effects of PHEXXI?

PHEXXI may cause serious side effects, including:

- Bladder infection (cystitis) and acute kidney infection (pyelonephritis). Urinary tract infections are common but can also be serious. You should not use PHEXXI if you have a history of urinary tract infections that keep coming back or other problems with your urinary tract. Call your healthcare provider if you have burning with urination or other signs and symptoms of a urinary tract infection such as: burning feeling when passing urine, urine that looks cloudy, pain in the pelvis, or back pain.
- Allergic reactions. Avoid using PHEXXI if you are a female who can become pregnant and are allergic to lactic acid, citric acid, potassium bitartrate or any of the ingredients in PHEXXI; or your sexual partners are allergic to any of the ingredients in PHEXXI". Stop using PHEXXI if you have a local vulvovaginal reaction.

The most common side effects of PHEXXI include:

- vaginal burning
- vaginal itching
- vaginal yeast infection

- discomfort around the vaginal area
- bacterial vaginosis

- vaginal discharge
- discomfort in the genital area
- pain while passing urine

These are not all the possible side effects of PHEXXI.

Call your healthcare provider for medical advice about side effects. You may report side effects to FDA at 1-800-FDA-1088.

How should I store PHEXXI?

- Store PHEXXI at room temperature between 68°F to 77°F (20°C to 25°C).
- Store PHEXXI in the original foil pouch.

Keep PHEXXI and all medicines out of the reach of children.

General information about the safe and effective use of PHEXXI.

Medicines are sometimes used for purposes other than those listed in a Patient Information leaflet. Do not use PHEXXI for a condition for which it was not prescribed. Do not give PHEXXI to other people, even if they have the same symptoms that you have. It may harm them.

You can ask your healthcare provider or pharmacist for information about PHEXXI that is written for health professionals.

What are the ingredients in PHEXXI?

Active ingredients: lactic acid, citric acid, and potassium bitartrate

Inactive ingredients: glycerin, alginic acid, xanthan gum, sodium hydroxide, benzoic acid, and purified water

For more information, go to www.phexxi.com or call 1-833-EVFMBIO.

Manufactured for Evofem, Inc., a wholly owned subsidiary of Evofem Biosciences, Inc.

©2023 Evofem, Inc. All rights reserved. Unless otherwise indicated, all trademarks used herein are the property of Evofem Biosciences, Inc.

This Patient Information has been approved by the U.S. Food and Drug Administration

Issued: June 2023

INSTRUCTIONS FOR USE

PHEXXI® (FEX ee)
(lactic acid, citric acid, and potassium bitartrate) vaginal gel

For Vaginal Use Only

These Instructions for Use contain information on how to use PHEXXI vaginal gel. Make sure that you read, understand, and follow the Instructions for Use before using PHEXXI and each time you get a refill. There may be new information.

Contents:

- Each box contains either 3 or 12 foil pouches.
- Each foil pouch contains a pre-filled applicator and plunger rod (see Figure A).
- Each pre-filled applicator contains 1 dose of PHEXXI for 1-time use (single use).

Figure A

Important Information You Need to Know Before Using PHEXXI

- Use 1 dose of PHEXXI within 1 hour before you have vaginal sex.
- A new PHEXXI pre-filled applicator must be used each time you have vaginal sex. If you have vaginal sex more than 1 time within 1 hour, a new PHEXXI pre-filled applicator must be used.

Prepare to Use PHEXXI

Keep the pre-filled applicator and plunger rod in the foil pouch until you are ready to use PHEXXI.

Step 1: Wash Your Hands

- Wash your hands with soap and water before opening the foil pouch.

Step 2: Remove the Pre-filled Applicator and Plunger Rod from the Foil Pouch

- Remove the pre-filled applicator and plunger rod from the foil pouch (see Figure B).

Figure B

Important: Do not remove the pink cap until instructed in Step 4.

Insert PHEXXI Gel

Step 3: Insert the Plunger Rod

- Gently and slowly insert the plunger rod into the pre-filled applicator. Push until you feel the tip of the plunger rod connect to the inside of the pre-filled applicator (see Figure C).
- Do not push hard or continue to push after the tip of the plunger rod connects to the inside of the pre-filled applicator. This could cause the gel to go into the pink cap.
- Use a new pre-filled applicator if the gel goes into the pink cap.

Figure C

Step 4: Remove the Pink Cap

- After the plunger rod is connected to the pre-filled applicator, remove the pink cap from the pre-filled applicator (see Figure D).
- The extra space between the gel and the end of the pre-filled applicator is normal.
- The pre-filled applicator is now ready for use.

Figure D

Step 5: Insert the PHEXXI Pre-filled Applicator into the Vagina

- Hold the pre-filled applicator at the grooved area closest to the plunger rod (see Figure E).
- Gently insert the pre-filled applicator into the vagina as far as it will comfortably go while you continue to hold it by the grooved area firmly. This can be done sitting with your knees apart, lying on your back with your knees bent (see Figure F), or while standing with your feet apart or knees bent.

Figure E

Figure F

Step 6: Insert PHEXXI Gel

- While the pre-filled applicator is inserted in your vagina, use your index finger to push the plunger rod down until it stops. This is to make sure you receive the entire dose of PHEXXI (see Figure G).
- It is normal for a small amount of gel to be left in the applicator. You will still get the right dose.

Figure G

Step 7: Remove the Used PHEXXI Pre-filled Applicator

- Gently remove the plunger rod and pre-filled applicator from the vagina (see Figure H) and throw away (dispose of) the used pre-filled applicator.
- PHEXXI should be used within 1 hour before each time you have vaginal sex. Use a new pre-filled applicator if you do not have vaginal sex within 1 hour of inserting PHEXXI gel and you still plan to have vaginal sex.

Figure H

Disposing of PHEXXI

Step 8: Throw Away (Dispose of) the Used PHEXXI Pre-filled Applicator

- Used PHEXXI pre-filled applicators and caps should be disposed of in the trash. The cap may be a potential choking hazard.

Storing PHEXXI

- Store PHEXXI at room temperature between 68°F to 77°F (20°C to 25°C).
- Store PHEXXI in the original foil pouch.

Keep PHEXXI and all medicines out of the reach of children.

These Instructions for Use have been approved by the U.S. Food and Drug Administration.

For more information, including full prescribing information and information on patient safety, go to www.phexxi.com or call 1-833-EVFMBIO.

Manufactured for Evofem, Inc., a wholly owned subsidiary of Evofem Biosciences, Inc.
©2023 Evofem, Inc. All rights reserved.

Issued: June 2023

PRINCIPAL DISPLAY PANEL - 12 Applicator Box

phexxi™

(lactic acid, citric acid, and
potassium bitartrate) Vaginal Gel
1.8%, 1%, 0.4%

NDC 69751-100-12
PN-5011